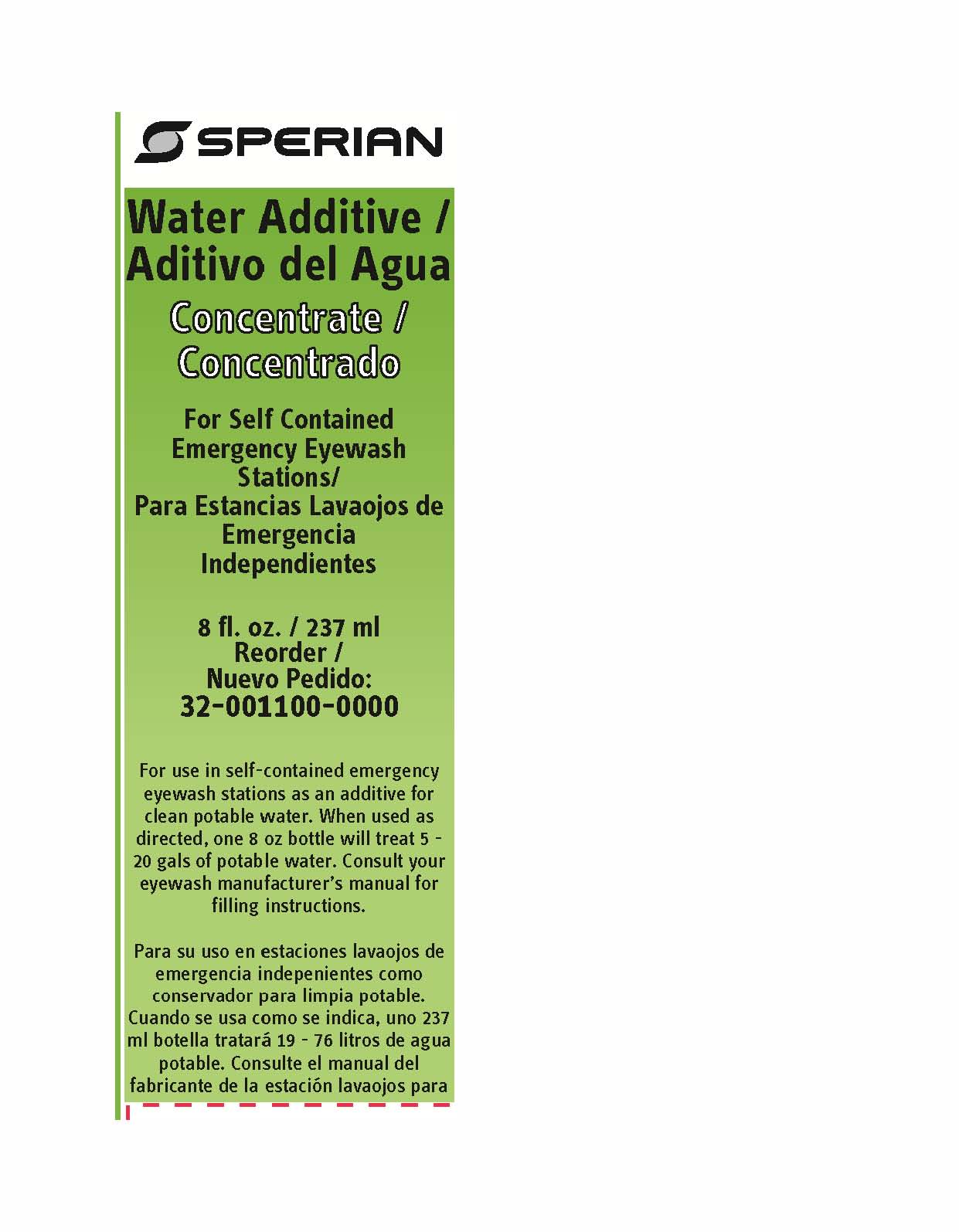 DRUG LABEL: Water Additive
NDC: 64809-105 | Form: LIQUID
Manufacturer: Sperian Eye & Face Protection Inc
Category: otc | Type: HUMAN OTC DRUG LABEL
Date: 20180321

ACTIVE INGREDIENTS: WATER 99 mL/100 mL
INACTIVE INGREDIENTS: CHLORHEXIDINE GLUCONATE

Sperian Water Additive

Active ingredient

Purified water

Purpose

Flushing Agent

Uses

For flushing the eye to reduce the chance of severe injury caused by acid, alkali, or particulate contamination.

Warnings

- For external use only
- To avoid contamination do not touch tip of container to any surface

Do not use

- in concentrated form
- while wearing contact lenses
- if solution changes color or becomes cloudy
- for injection
- in intraocular surgery
- internally

Ask a doctor if you have

- eye pain
- changes in vision
- redness or irritation of eye after use
- an injury caused by an alkali

Keep out of reach of children

If swallowed, get medical help or contact a Poison Control Center right away.

Directions

Mix additive with potable water as follows:

- Wear protective eyewear and gloves
- Follow sanitary procedures
- Thoroughly clean portable eyewash station and rinse with potable water
- Use a clean container of sufficient capacity to mix enough solution to fill eyewash station. Solution may be mixed directly in eyewash station
- Add entire contents of the bottle to the container
- Fill the station to the manufacturer's required level and mix or agitate thoroughly
- Date station inspection
- Station should be cleaned and refilled every 120 days when using this product
- Properly dispose of empty bottles after use. D o not reuse.

Other information

- Do not use is seal is broken
- Do not freeze
- Do not use if eye is lacerated or object is embedded
- For use in emergency eyewash stations only
- Mix per directions
- Sperian Water Additive must not be used undiluted or in solution for any other purpose
- Do NOT add any other chemicals or materials to this solution
- Avoid contact with skin
- Store between 35oF - 100oF (2oC - 38oC)

Inactive ingredients

chlorhexidine digluconate

Questions?

Call 1-800-336-3255

Sperian Eye & Face Protection, Inc.

825 East Highway 151

Plattville, WI 53818 USA